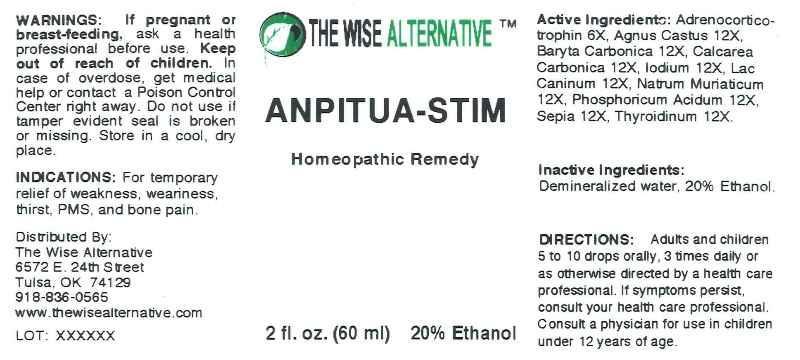 DRUG LABEL: Anpitua Stim
NDC: 51096-0006 | Form: LIQUID
Manufacturer: J and Health DBA Wise Alternative
Category: homeopathic | Type: HUMAN OTC DRUG LABEL
Date: 20111215

ACTIVE INGREDIENTS: CORTICOTROPIN 6 [hp_X]/1 mL; CHASTE TREE 12 [hp_X]/1 mL; BARIUM CARBONATE 12 [hp_X]/1 mL; OYSTER SHELL CALCIUM CARBONATE, CRUDE 12 [hp_X]/1 mL; IODINE 12 [hp_X]/1 mL; CANIS LUPUS FAMILIARIS MILK 12 [hp_X]/1 mL; SODIUM CHLORIDE 12 [hp_X]/1 mL; PHOSPHORIC ACID 12 [hp_X]/1 mL; SEPIA OFFICINALIS JUICE 12 [hp_X]/1 mL; THYROID, PORCINE 12 [hp_X]/1 mL
INACTIVE INGREDIENTS: WATER; ALCOHOL

Drug Facts

ACTIVE INGREDIENTS:

Adrenocorticotrophin 6X, Agnus castus 12X, Baryta carbonica 12X, Calcarea carbonica 12X, Iodium 12X, Lac caninum 12X, Natrum muriaticum 12X, Phosphoricum acidum 12X, Sepia 12X, Thyrodinium 12X.

INDICATIONS

For temporary relief of weakness, weariness, thirst, PMS, and bone pain.

WARNINGS

If pregnant or breast-feeding, ask a health professional before use.

Keep out of reach of children. In case of overdose, get medical help or contact a Poison Control Center right away.

Do not use if tamper evident seal is broken or missing.

Store in a cool, dry place.

DIRECTIONS

Adults and children 5 to 10 drops orally 3 times daily or as otherwise directed by health care professional. If symptoms persist, consult your health care professional. Consult a physician for use in children 12 years of age.

INACTIVE INGREDIENTS

Demineralized water, 20% Ethanol.

KEEP OUT OF REACH OF CHILDREN

In case of overdose, get medical help or contact a Poison Control Center right away.

INDICATIONS

For temporary relief of weakness, weariness, thirst, PMS, and bone pain.

QUESTIONS

Dist. By:

J and L Health LLC

6572 E. 24th St

Tulsa, OK 74129

918-836-0565

www.thewisealternative.com

PACKAGE LABEL

THE WISE ALTERNATIVE

ANPITUA STIM

Homeopathic Remedy

2 fl oz (60 ml)